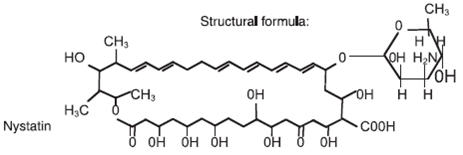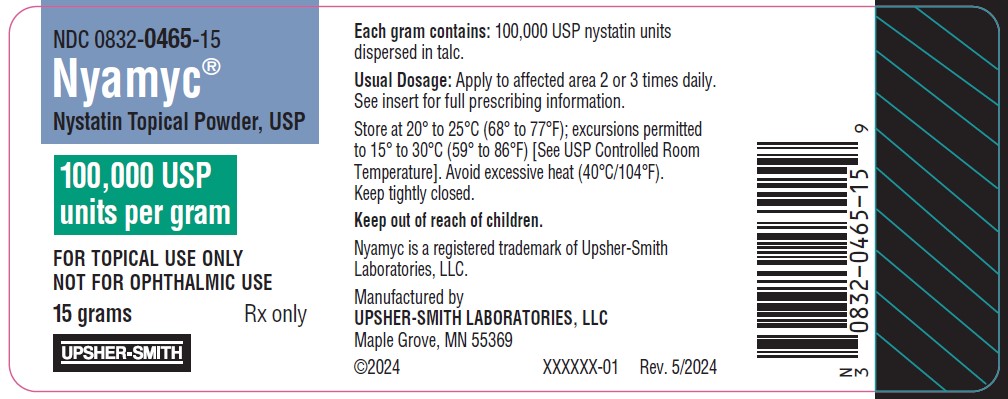 DRUG LABEL: Nyamyc
NDC: 0832-0465 | Form: POWDER
Manufacturer: Upsher-Smith Laboratories, LLC
Category: prescription | Type: HUMAN PRESCRIPTION DRUG LABEL
Date: 20250709

ACTIVE INGREDIENTS: NYSTATIN 100000 [USP'U]/1 g
INACTIVE INGREDIENTS: TALC

Nyamyc®
(Nystatin Topical Powder, USP)

100,000 units per gram
Rx only

FOR TOPICAL USE ONLY • NOT FOR OPHTHALMIC USE

DESCRIPTION

Nystatin is a polyene antifungal antibiotic obtained from Streptomyces nursei.

Nyamyc®(Nystatin Topical Powder, USP) is for dermatologic use.

Nyamyc®(Nystatin Topical Powder, USP) contains 100,000 USP nystatin units per gram dispersed in talc.

CLINICAL PHARMACOLOGY

Pharmacokinetics

Nystatin is not absorbed from intact skin or mucous membrane.

Microbiology

Nystatin is an antibiotic which is both fungistatic and fungicidal in vitroagainst a wide variety of yeasts and yeast-like fungi, including Candida albicans, C. parapsilosis, C. tropicalis, C. guilliermondi, C. pseudotropicalis, C. krusei, Torulopsis glabrata, Tricophyton rubrum, T. mentagrophytes.

Nystatin acts by binding to sterols in the cell membrane of susceptible species resulting in a change in membrane permeability and the subsequent leakage of intracellular components. On repeated subculturing with increasing levels of nystatin, Candida albicansdoes not develop resistance to nystatin. Generally, resistance to nystatin does not develop during therapy. However, other species of Candida (C. tropicalis, C. guilliermondi, C. krusei, and C. stellatoides)become quite resistant on treatment with nystatin and simultaneously become cross resistant to amphotericin as well. This resistance is lost when the antibiotic is removed.

Nystatin exhibits no appreciable activity against bacteria, protozoa, or viruses.

INDICATIONS AND USAGE

Nyamyc®(Nystatin Topical Powder, USP) is indicated in the treatment of cutaneous or mucocutaneous mycotic infections caused by Candida albicansand other susceptible Candidaspecies.

Nyamyc® (Nystatin Topical Powder, USP) is not indicated for systemic, oral, intravaginal or ophthalmic use.

CONTRAINDICATIONS

Nyamyc®(Nystatin Topical Powder, USP) is contraindicated in patients with a history of hypersensitivity to anyof its components.

PRECAUTIONS

General

Nyamyc® (Nystatin Topical Powder, USP) should not be used for the treatment of systemic, oral, intravaginal or ophthalmic infections.

If irritation or sensitization develops, treatment should be discontinued and appropriate measures taken as indicated. It is recommended that KOH smears, cultures, or other diagnostic methods be used to confirm the diagnosis of cutaneous or mucocutaneous candidiasis and to rule out infection caused by other pathogens.

INFORMATION FOR THE PATIENT

Patients using this medication should receive the following information and instructions:

1. The patient should be instructed to use this medication as directed (including the replacement of missed doses). This medication is not for any disorder other than that for which it is prescribed.
2. Even if symptomatic relief occurs within the first few days of treatment, the patient should be advised not to interrupt or discontinue therapy until the prescribed course of treatment is completed.
3. If symptoms of irritation develop, the patient should be advised to notify the physician promptly.

Laboratory Tests

If there is a lack of therapeutic response, KOH smears, cultures, or other diagnostic methods should be repeated.

Carcinogenesis, Mutagenesis, Impairment of Fertility

No long-term animal studies have been performed to evaluate the carcinogenic potential of nystatin. No studies have been performed to determine the mutagenicity of nystatin or its effects on male or female fertility.

Pregnancy

Teratogenic Effects

Animal reproduction studies have not been conducted with any nystatin topical preparation. It also is not known whether theses preparations can cause fetal harm when used by a pregnant woman or can affect reproductive capacity. Nyamyc®(Nystatin Topical Powder, USP) should be prescribed for a pregnant woman only if the potential benefit to the mother outweighs the potential risk to the fetus.

Nursing Mothers

It is not known whether nystatin is excreted in human milk. Caution should be exercised when nystatin is prescribed for a nursing woman.

Pediatric Use

Safety and effectiveness have been established in the pediatric population from birth to 16 years. [see DOSAGE AND ADMINISTRATION].

Geriatric Use

Clinical studies with nystatin topical powder did not include sufficient numbers of subjects aged 65 years and older to determine whether they respond differently than younger subjects. Other reported clinical experience has not identified differences in responses between elderly and younger patients, but greater sensitivity of some older individuals cannot be ruled out.

ADVERSE REACTIONS

The frequency of adverse events reported in patients using nystatin topical preparations is less than 0.1%. The more common events that were reported include allergic reactions, burning, itching, rash, eczema, and pain on application. [see PRECAUTIONS: General].

DOSAGE AND ADMINISTRATION

Very moist lesions are best treated with the topical dusting powder.

Adults and Pediatric Patients (Neonates and Older)

Apply to candidal lesions two or three times daily until healing is complete. For fungal infection of the feet caused by Candidaspecies, the powder should be dusted on the feet, as well as, in all foot wear.

HOW SUPPLIED

Nyamyc® (Nystatin Topical Powder, USP)100,000 units nystatin per gram is available as follow:

Bottles of 15 g | (NDC 0832-0465-15)
Bottles of 30 g | (NDC 0832-0465-30)
Bottles of 60 g | (NDC 0832-0465-60)

STORAGE

Nyamyc® (Nystatin Topical Powder, USP)

Store at 20° to 25°C (68° to 77°F); excursions permitted to 15° to 30°C (59° to 86°F) [See USP Controlled Room Temperature]. Avoid excessive heat (40°C/104°F). Keep tightly closed. Keep out of reach of children.

Nyamyc is a registered trademark of Upsher-Smith Laboratories, LLC.

Manufactured by
UPSHER-SMITH LABORATORIES, LLC
Maple Grove, MN 55369

Revised: 6/2024

PRINCIPAL DISPLAY PANEL - 15 gram Bottle Carton

NDC 0832-0465-15
Nyamyc®
Nystatin Topical Powder, USP

100,000 USP
units per gram

FOR TOPICAL USE ONLY.
NOT FOR OPHTHALMIC USE.

NET WT. 15 grams
Rx only

UPSHER-SMITH